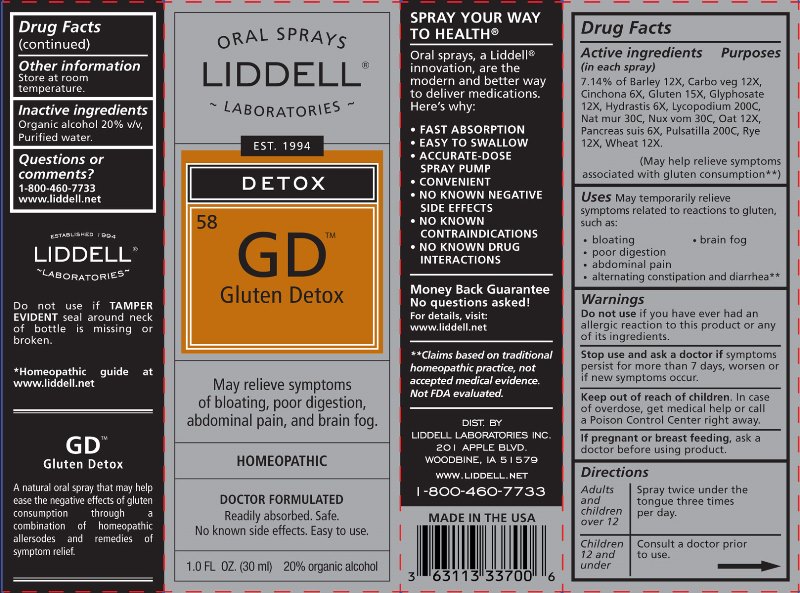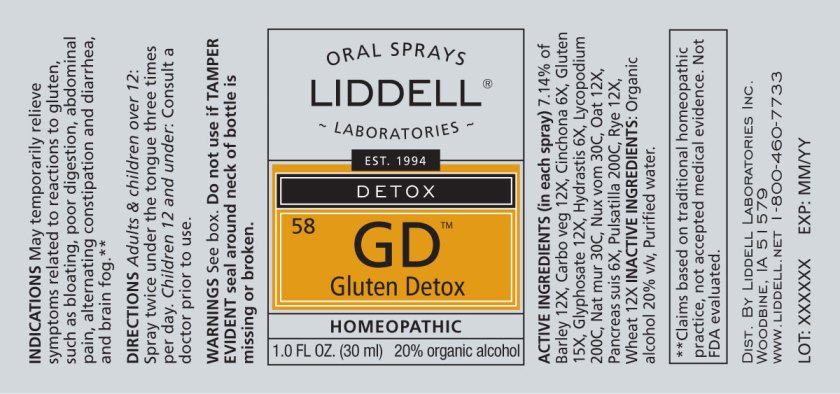 DRUG LABEL: Gluten Detox
NDC: 50845-0234 | Form: LIQUID
Manufacturer: Liddell Laboratories, Inc.
Category: homeopathic | Type: HUMAN OTC DRUG LABEL
Date: 20241104

ACTIVE INGREDIENTS: BARLEY 12 [hp_X]/1 mL; ACTIVATED CHARCOAL 12 [hp_X]/1 mL; CINCHONA OFFICINALIS BARK 6 [hp_X]/1 mL; WHEAT GLUTEN 15 [hp_X]/1 mL; GLYPHOSATE 12 [hp_X]/1 mL; GOLDENSEAL 6 [hp_X]/1 mL; LYCOPODIUM CLAVATUM SPORE 200 [hp_C]/1 mL; SODIUM CHLORIDE 30 [hp_C]/1 mL; STRYCHNOS NUX-VOMICA SEED 30 [hp_C]/1 mL; OATMEAL 12 [hp_X]/1 mL; SUS SCROFA PANCREAS 6 [hp_X]/1 mL; PULSATILLA VULGARIS WHOLE 200 [hp_C]/1 mL; RYE 12 [hp_X]/1 mL; WHEAT 12 [hp_X]/1 mL
INACTIVE INGREDIENTS: WATER; ALCOHOL

DRUG FACTS:

ACTIVE INGREDIENTS:

(in each spray) 7.14% of Barley (Grain) 12X, Carbo Vegetabilis 12X, Cinchona Officinalis 6X, Gluten 15X, Glyphosate 12X, Hydrastis Canadensis 6X, Lycopodium Clavatum 200C, Natrum Muriaticum 30C, Nux Vomica 30C, Oat (Grain) 12X, Pancreas Suis 6X, Pulsatilla (Vulgaris) 200C, Rye (Grain) 12X, Wheat (Grain) 12X.

INDICATIONS:

May temporarily relieve symptoms related to reactions to gluten, such as:

• bloating

• brain fog

• poor digestion

• abdominal pain

• alternating constipation and diarrhea**

**Claims based on traditional homeopathic practice, not accepted medical evidence. Not FDA evaluated.

WARNINGS:

Do not use if you have ever had an allergic reaction to this product or any of its ingredients.

Stop use and ask a doctor if symptoms persist, worsen or if new symptoms occur.

Keep out of reach of children. In case of overdose, get medical help or call a Poison Control Center right away.

If pregnant or breast feeding, ask a doctor before use.

Do not use if TAMPER EVIDENT seal around neck of bottle is missing or broken.

Keep out of reach of children. In case of overdose, get medical help or call a Poison Control Center right away.

DIRECTIONS:

Adults and children over 12: Spray twice under the tongue three times per day.

Children 12 and under: Consult a doctor prior to use.

INDICATIONS:

May temporarily relieve symptoms related to reactions to gluten, such as:

• bloating

• brain fog

• poor digestion

• abdominal pain

• alternating constipation and diarrhea**

**Claims based on traditional homeopathic practice, not accepted medical evidence. Not FDA evaluated.

INACTIVE INGREDIENTS:

Organic alcohol 20% v/v, Purified water.

QUESTIONS:

DIST. BY

LIDDELL LABORATORIES INC.

201 APPLE BLVD.

WOODBINE, IA 51579

WWW.LIDDELL.NET

1-800-460-7733

PACKAGE LABEL DISPLAY:

ORAL SPRAYS

LIDDELL

LABORATORIES

EST. 1994

DETOX

^58 GD

Gluten Detox

May relieve symptoms

of bloating, poor digestion,

abdominal pain, and brain fog

HOMEOPATHIC

DOCTOR FORMULATED

Readily absorbed. Safe.

No known side effects. Easy to use

1.0 FL. OZ. (30 ml)